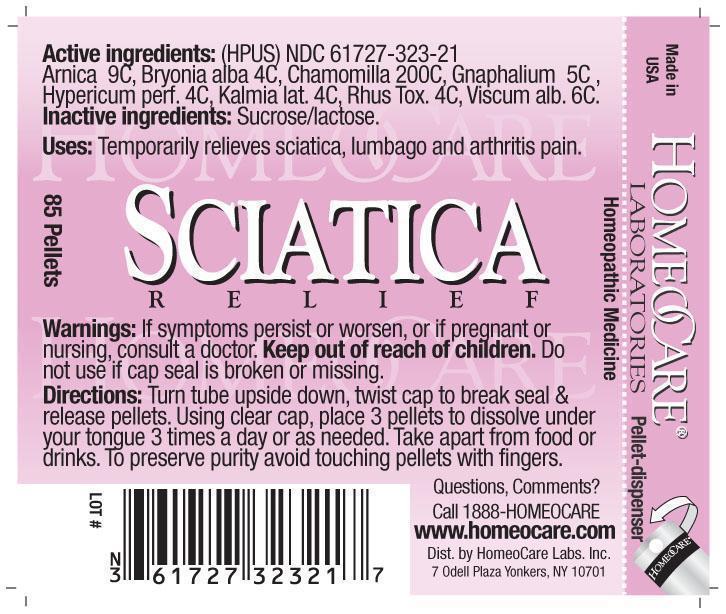 DRUG LABEL: Sciatica Relief
NDC: 61727-323 | Form: PELLET
Manufacturer: Homeocare Laboratories
Category: homeopathic | Type: HUMAN OTC DRUG LABEL
Date: 20181231

ACTIVE INGREDIENTS: ARNICA MONTANA FLOWER 9 [hp_C]/4 g; BRYONIA ALBA WHOLE 4 [hp_C]/4 g; MATRICARIA RECUTITA 200 [hp_C]/4 g; PSEUDOGNAPHALIUM LUTEOALBUM LEAF 5 [hp_C]/4 g; HYPERICUM PERFORATUM 4 [hp_C]/4 g; KALMIA LATIFOLIA LEAF 4 [hp_C]/4 g; TOXICODENDRON PUBESCENS LEAF 4 [hp_C]/4 g; VISCUM ALBUM LEAF 6 [hp_C]/4 g
INACTIVE INGREDIENTS: SUCROSE; LACTOSE

Sciatica Relief

Active ingredients:

Arnica 9C, Bryonia alba 4C, Chamomilla 200C, Gnaphallium 5C, Hypericum perf. 4C, Kalmia lat. 4C, Rhus Tox. 4C, Viscum alb. 6C.

Inactive ingredients:

Sucrose/lactose.

Purpose:

Temporarily relieves sciatica, lumbago and arthritis pain.

Keep out of reach of children.

Warnings:

If symptoms persist or worsen, or if pregnant or nursing, consult a doctor. Keep out of reach of children. Do not use if cap seal is broken or missing.

Indications & Usage:

Turn tube upside down, twist cap to break seal & release pellets. Using clear cap, place 3 pellets to dissolve under our tongue 3 times a day or as needed. Take apart from food or drinks. To preserve purity avoid touching pellet with fingers.

Dosage & Administration:

Turn tube upside down, twist cap to break seal & release pellets. Using clear cap, place 3 pellets to dissolve under our tongue 3 times a day or as needed. Take apart from food or drinks. To preserve purity avoid touching pellet with fingers.

Sciatica Relief

Homeopathic Medicine

85 Pellets

hcl_label_sciatica 2012.jpg